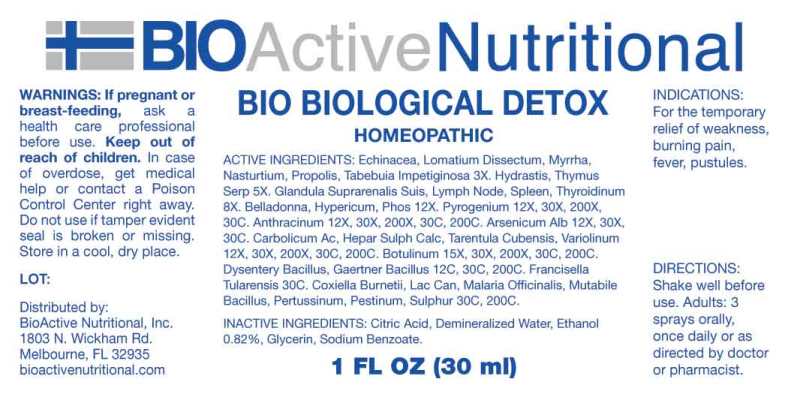 DRUG LABEL: Bio Biological Detox
NDC: 43857-0464 | Form: SPRAY
Manufacturer: BioActive Nutritional, Inc.
Category: homeopathic | Type: HUMAN OTC DRUG LABEL
Date: 20251006

ACTIVE INGREDIENTS: ECHINACEA ANGUSTIFOLIA WHOLE 3 [hp_X]/1 mL; LOMATIUM DISSECTUM ROOT 3 [hp_X]/1 mL; MYRRH 3 [hp_X]/1 mL; NASTURTIUM OFFICINALE 3 [hp_X]/1 mL; PROPOLIS WAX 3 [hp_X]/1 mL; TABEBUIA IMPETIGINOSA BARK 3 [hp_X]/1 mL; GOLDENSEAL 5 [hp_X]/1 mL; THYMUS SERPYLLUM WHOLE 5 [hp_X]/1 mL; SUS SCROFA ADRENAL GLAND 8 [hp_X]/1 mL; SUS SCROFA LYMPH 8 [hp_X]/1 mL; SUS SCROFA SPLEEN 8 [hp_X]/1 mL; THYROID 8 [hp_X]/1 mL; ATROPA BELLADONNA 12 [hp_X]/1 mL; HYPERICUM PERFORATUM WHOLE 12 [hp_X]/1 mL; PHOSPHORUS 12 [hp_X]/1 mL; RANCID BEEF 12 [hp_X]/1 mL; BACILLUS ANTHRACIS IMMUNOSERUM RABBIT 12 [hp_X]/1 mL; ARSENIC TRIOXIDE 12 [hp_X]/1 mL; PHENOL 12 [hp_X]/1 mL; CALCIUM SULFIDE 12 [hp_X]/1 mL; CITHARACANTHUS SPINICRUS 12 [hp_X]/1 mL; VACCINIA VIRUS STRAIN NEW YORK CITY BOARD OF HEALTH LIVE ANTIGEN 12 [hp_X]/1 mL; BOTULINUM TOXIN TYPE A 15 [hp_X]/1 mL; SHIGELLA DYSENTERIAE 12 [hp_C]/1 mL; SALMONELLA ENTERICA ENTERICA SEROVAR ENTERITIDIS 12 [hp_C]/1 mL; FRANCISELLA TULARENSIS 30 [hp_C]/1 mL; COXIELLA BURNETII 30 [hp_C]/1 mL; CANIS LUPUS FAMILIARIS MILK 30 [hp_C]/1 mL; PLASMODIUM MALARIAE 30 [hp_C]/1 mL; ESCHERICHIA COLI 30 [hp_C]/1 mL; HUMAN SPUTUM, BORDETELLA PERTUSSIS INFECTED 30 [hp_C]/1 mL; YERSINIA PESTIS 30 [hp_C]/1 mL; SULFUR 30 [hp_C]/1 mL
INACTIVE INGREDIENTS: WATER; GLYCERIN; SODIUM BENZOATE; CITRIC ACID MONOHYDRATE; ALCOHOL

DRUG FACTS:

ACTIVE INGREDIENTS:

Echinacea (Angustifolia) 3X, Lomatium Dissectum 3X, Myrrha 3X, Nasturtium Aquaticum 3X, Propolis 3X, Tabebuia Impetiginosa 3X, Hydrastis Canadensis 5X, Thymus Serpyllum 5X, Glandula Suprarenalis Suis 8X, Lymph Node (Suis) 8X, Spleen (Suis) 8X, Thyroidinum (Suis) 8X, Belladonna 12X, Hypericum Perforatum 12X, Phosphorus 12X, Pyrogenium 12X, 30X, 200X, 30C, Anthracinum 12X, 30X, 200X, 30C, 200C, Arsenicum Album 12X, 30X, 30C, Carbolicum Acidum 12X, 30X, 200X, 30C, 200C, Hepar Sulphuris Calcareum 12X, 30X, 200X, 30C, 200C, Tarentula Cubensis 12X, 30X, 200X, 30C, 200C, Variolinum 12X, 30X, 200X, 30C, 200C, Botulinum 15X, 30X, 200X, 30C, 200C, Dysentery Bacillus 12C, 30C, 200C, Gaertner Bacillus 12C, 30C, 200C, Francisella Tularensis 30C, Coxiella Burnetii 30C, 200C, Lac Caninum 30C, 200C, Malaria Officinalis 30C, 200C, Mutabile Bacillus 30C, 200C, Pertussinum 30C, 200C, Pestinum 30C, 200C, Sulphur 30C, 200C.

INDICATIONS:

For the temporary relief of weakness, burning pain, fever, pustules.

WARNINGS:

If pregnant or breast-feeding, ask a health care professional before use.
Keep out of reach of children. In case of overdose, get medical help or contact a Poison Control Center right away.
Do not use if tamper evident seal is broken or missing.
Store in cool, dry place.

Keep out of reach of children. In case of overdose, get medical help or contact a Poison Control Center right away.

DIRECTIONS:

Shake well before use. Adults: 3 sprays orally, once daily or as directed by doctor or pharmacist.

INDICATIONS:

For the temporary relief of weakness, burning pain, fever, pustules.

INACTIVE INGREDIENTS:

Citric Acid, Demineralized Water, Ethanol 0.82%, Glycerin, Sodium Benzoate.

QUESTIONS:

Distributed by:
BioActive Nutritional, Inc.
1803 N. Wickham Rd.
Melbourne, FL 32935
bioactivenutritional.com

PACKAGE LABEL DISPLAY:

BIOActive Nutritional
BIO BIOLOGICAL DETOX
HOMEOPATHIC
1 FL OZ (30 ml)